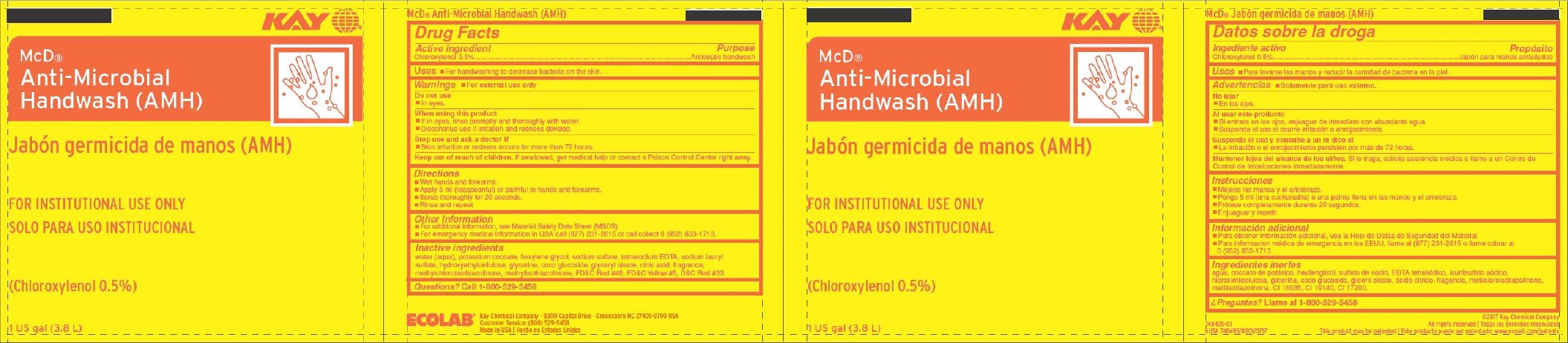 DRUG LABEL: Kay McD Anti-Microbial Handwash
NDC: 47593-668 | Form: SOLUTION
Manufacturer: Ecolab Inc.
Category: otc | Type: HUMAN OTC DRUG LABEL
Date: 20251212

ACTIVE INGREDIENTS: CHLOROXYLENOL 0.5 mg/100 mL
INACTIVE INGREDIENTS: WATER; POTASSIUM COCOATE; HEXYLENE GLYCOL; SODIUM SULFATE ANHYDROUS; EDETATE SODIUM; SODIUM LAURYL SULFATE; HYDROXYETHYL CELLULOSE (3000 MPA.S AT 1%); GLYCERIN; DECYL GLUCOSIDE; ANHYDROUS CITRIC ACID; METHYLCHLOROISOTHIAZOLINONE; METHYLISOTHIAZOLINONE; FD&C RED NO. 40; FD&C YELLOW NO. 5; D&C RED NO. 33

Drug Facts

Active ingredient

Chloroxylenol 0.5%

Purpose

Antiseptic handwash

Uses

- For handwashing to decrease bacteria on the skin.

Warnings

- For external use only

Do not use

- In eyes.

When using this product

- If in eyes, rinse promptly and thoroughly with water.
- Discontinue use if irritation and redness develop.

Stop use and ask a doctor if

- Skin irritation and redness occurs for more than 72 hours.

Keep out of reach of children. If swallowed, get medical help or contact a Poison Control Center right away.

Directions

- Wet hands and forearms.
- Apply 5 ml (teaspoonful) or palmful to hands and forearms.
- Scrub thoroughly for 20 seconds.
- Rinse and repeat.

Other information

- For additional information, see Material Safety Data Sheet (MSDS)
- For emergency medical information in USA call (877) 231-2615 or call collect 0 (952)853-1713.

Inactive ingredients

water (aqua), potassium cocoate, hexylene glycol, sodium sulfate, tetrasodium EDTA, sodium lauryl sulfate, hydroxyethylcellulose, glycerine, coco glucoside, glyceryl oleate, citric acid, fragrance, methylchloroisothiazolinone, methylisothiazolinone, FD&C Red 40, FD&C Yellow 5, D&C Red 33.

Questions?

Call 1-800-529-5458

Principal Display Panel - Representative Label

McD

Anti-Microbial

Handwash (AMH)

FOR INSTITUTIONAL USE ONLY

(Chloroxylenol 0.5%)

1 US gal (3.8L)

ECOLAB

KAY CHEMICAL COMPANY - 8300 Capital Drive - Greensboro, NC 27409-9790 USA

Customer Service: (800) 529-5458

Made in USA